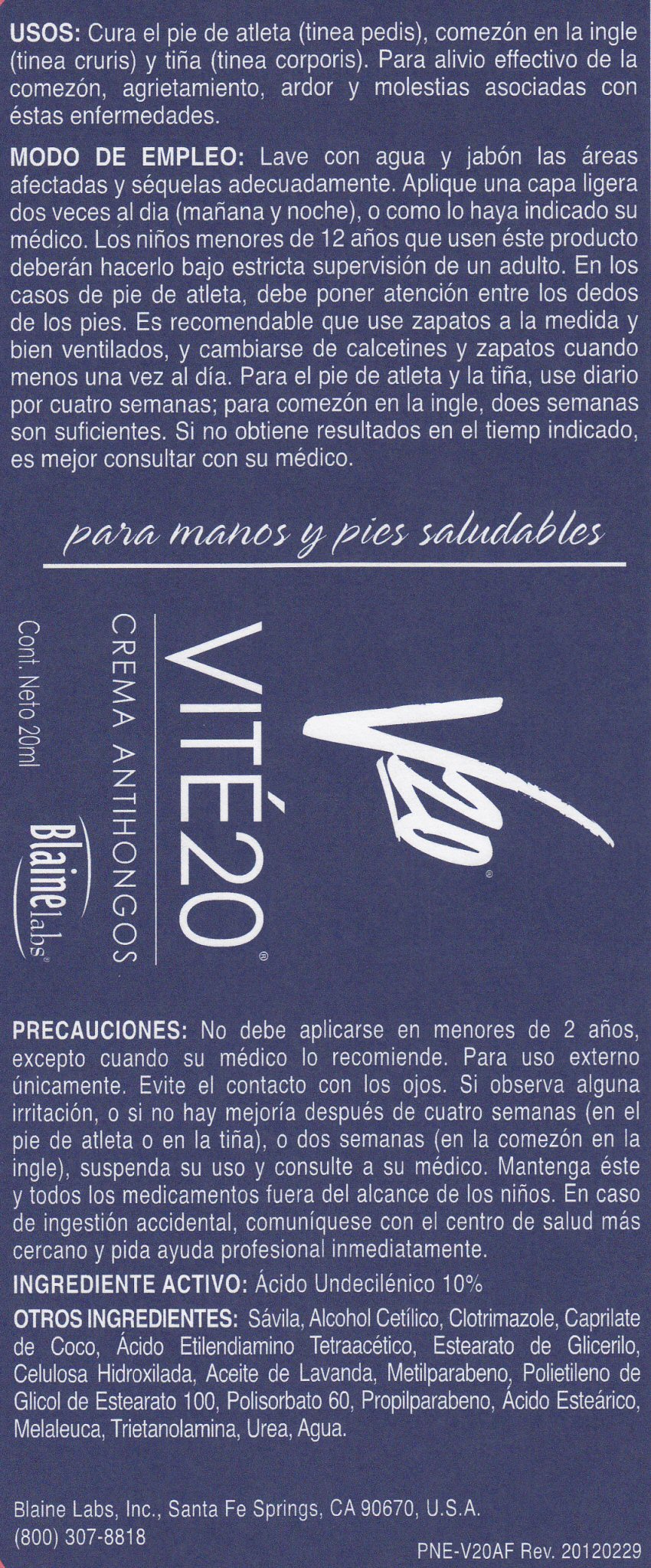 DRUG LABEL: Vite20
NDC: 63347-800 | Form: CREAM
Manufacturer: Blaine Labs Inc.
Category: otc | Type: HUMAN OTC DRUG LABEL
Date: 20241224

ACTIVE INGREDIENTS: UNDECYLENIC ACID 2 mg/20 mL
INACTIVE INGREDIENTS: ALOE VERA LEAF; CETYL ALCOHOL; CLOTRIMAZOLE; COCO-CAPRYLATE; EDETATE DISODIUM; GLYCERYL MONOSTEARATE; HYDROXYETHYL CELLULOSE (5000 MPA.S AT 1%); LAVENDER OIL; METHYLPARABEN; PEG-100 STEARATE; POLYSORBATE 60; PROPYLPARABEN; STEARIC ACID; TEA TREE OIL; TROLAMINE; UREA; WATER

Ingrediente Activo Active Ingredients

INGREDIENTE ACTIVO: Acido Undecilenico 10 %

Active Ingredient: Undecylenic Acid 10%

Purpose

CREMA ANTIHONGOS

Antifungal Cream

Precauciones Keep Out Of Reach Of Children

Mantenga este y todos los medicamentos fuera del alcance de los ninos. En caso de ingestion accidental, comuniquese con el centro de salud mas cercano y pida ayuda profesional inmediatamente.

Keep this and all drugs out of reach of children. In case of accidental ingestion, seek professional assistance or contact a Poison Control Center immediately.

Usos USES

USOS: Cura el pie de (tinea pedis), comezon en la ingle (tinea cruris) y tina (tinea corporis). Par alivio effectivo de la comezon, agrietamiento, ardor y molestias asociadas con estas enfermedades.

USES:Cures athlete's foot (tinea pedis), jock itch (tinea cruris) and ringworm(tinea corpois). For effective relief of itching, cracking, burning and discomfort that can accompany these conditions.

Precauciones Warnings

PRECAUCIONES: No debe aplicarse en menores de 2 anos, excepto cuando su medico lo recomiende. Para uso externo unicamente. Evite el contacto con los olos. Si observa alguna irritacion, o si no hay mejoria despues de cuatro semanas (en el pie de atleta o en la tina), o dos semanas (en la comezon el la ingle), suspenda su uso y consulte a su medico. Mantenga este y todos los medicamentos fuera del alcance de los ninos. En caso de ingestion accidental, comuniquese con el centro de salud mas cercano y pida ayuda profesional inmediatamente.

WARNINGS: Do not use on children under 2 years of age unless directed by a physician. For external use only. Avoid contact with eyes. If irritation occurs or if there is no improvement within 4 weeks (for athlete's foot or ringworm) or within 2 weeks (for jock itch), discontinue use and consult a physician. Keep this and all drugs out of reach of children. In case of accidental ingestion, seek professional assistance or contact a Poison Control Center immediately.

Modo De Empleo Directions

MODO DE EMPLEO: Lave con aqua y jabon ;as areas afectadas y sequelas adecuadamente. Aplique una capa ligera dos veces al dia (manana y noche), o como lo haya indicado su medico. Los ninos menores de 12 anos que usen este producto deberan hacerlo bajo estricta supervision de un adulto. En los casos de pie de atleta, debe poner atencion entre los dedos de los pies. Es recomendable que use zapatos a la medida y bien ventilados, y cambiarse de calcentines y zapatos cuando menos una vez al dia. Para el pie de atleta y la tina, use diario por cuatro semanas; papa comezon en la ingle, does semanas son suficentes. Si no obtiene resultados en el tiemp indicado, es mejor consultar con su medico.

DIRECTIONS: wash the affected area with soap and water and dry thoroughly. Apply sparingly over affected area twice daily (morning and night), or as directed by a physician. For athlete's foot, pay special attention to spaces between the toes; wear well-fitting, ventilated shoes and change shoes and socks at least once daily. For athlete's foot and ringworm, use daily for 4 weeks; for jock itch, use daily for 2 weeks. If condition persists longer, consult a physician. This product is not effective on scalp or nails. Supervise children in the use of this product.

Otros Ingredientes Inactive Ingredients

OTROS INGREDIENTES: Savila, Alcohol Cetilico, Clotrimazole, Caprilate de Coco, Acido Etilendiamino Tetraacetico, Estearato de Glicerilo, Celulosa Hidroxilada, Aceite de Lavanda. Metilparabeno, Polietileno de Glicol de Estearato 100, Polisorbato 60, Propilparabeno, Acido Estearico, Melaleuca, Trietanolamina, Urea, Agua.

INACTIVE INGREDIENTS: Aloe Vera, Cetyl Alcohol, Clotrimazole, Coco-Caprylate/Caprate, Disodium EDTA, Glyceryl Stearic, Hydroxyethylcellulose, lavender Oil, Methylparaben, PEG-100 Stearate, Polysorbate 60, Propylparaben, Stearic Acid, Tea Tree Oil, Triethanolamine, Urea, Water.

Package Label

VITE20 CREMA ANIHONGOS

Cont. Neto 20 ml

para manos y pies saludables

Blaine labs, Inc. Santa Fe Springs, CA 90670, U.S.A. (800) 307-8818 PNE-V20AR Rev. 20120229